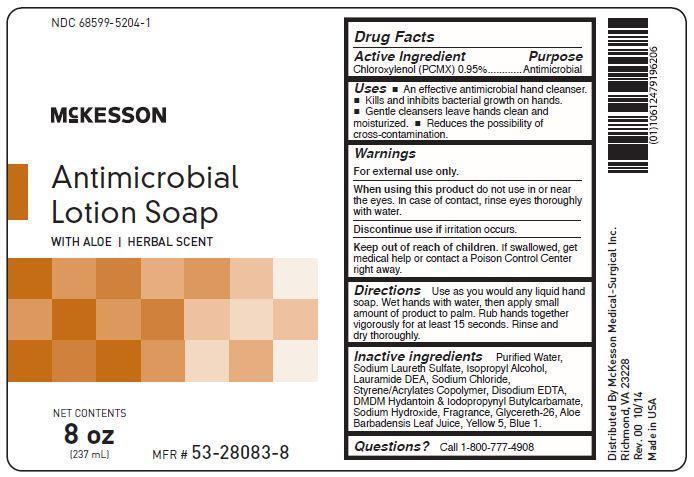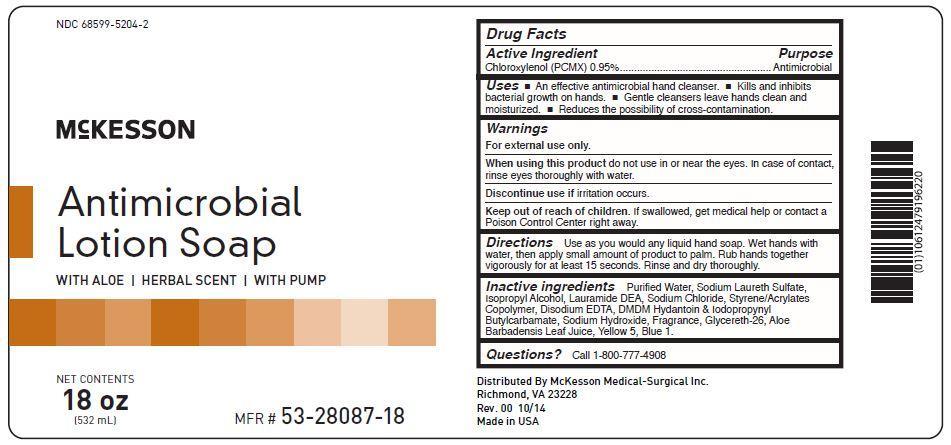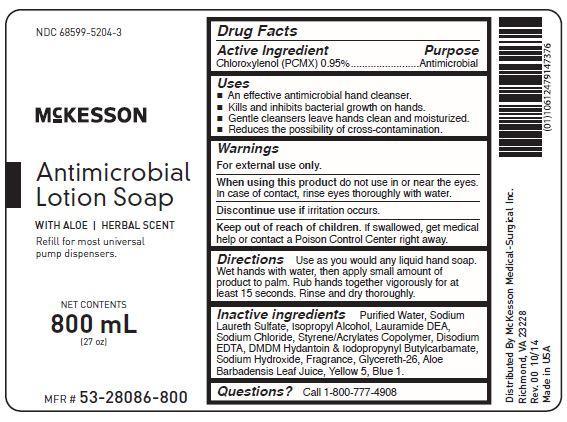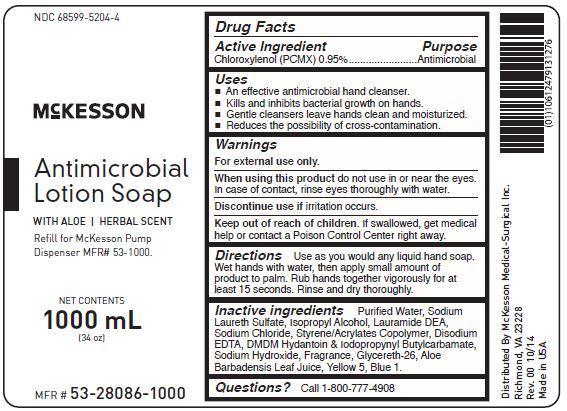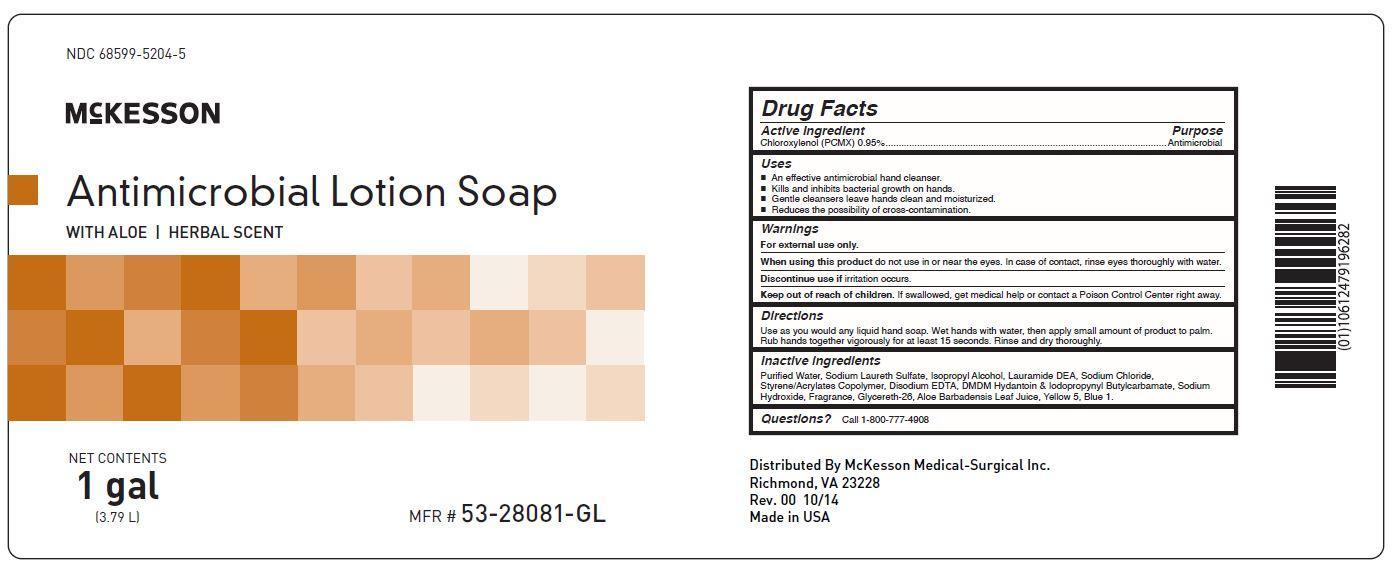 DRUG LABEL: Mckesson Hand Cleanse and Soothe with Aloe
NDC: 68599-5204 | Form: GEL
Manufacturer: Mckesson Medical-Surgical Inc.
Category: otc | Type: HUMAN OTC DRUG LABEL
Date: 20241010

ACTIVE INGREDIENTS: CHLOROXYLENOL 0.95 g/1 g
INACTIVE INGREDIENTS: WATER; SODIUM LAURETH SULFATE; ISOPROPYL ALCOHOL; LAURIC DIETHANOLAMIDE; SODIUM CHLORIDE; STYRENE/ACRYLAMIDE COPOLYMER (MW 500000); EDETATE DISODIUM; DMDM HYDANTOIN; IODOPROPYNYL BUTYLCARBAMATE; SODIUM HYDROXIDE; GLYCERETH-26; ALOE VERA LEAF; FD&C YELLOW NO. 5; FD&C BLUE NO. 1

Active Ingredient Purpose

Chloroxylenol (PCMX) 0.95% ................................. Antimicrobial

Uses

- an effective antimicrobial hand cleanser.
- kills and inhibits bacterial growth on hands.
- gentle cleansers leave hands clean and moisturized.
- reduces the possibility of cross-contamination.

Keep out of reach of children. If swallowed, get medical help or contact a Poison Control Center right away.

INDICATIONS AND USAGE

McKesson Antimicrobial Lotion Soap

With Aloe | Herbal Scent

Directions

Use as you would any liquid hand soap. Wet hands with water, then apply small amount of product to palm. Rub hands together vigorously for at least 15 seconds. Rinse and dry thoroughly.

Warnings

For external use only.

When using this product do not use in or near the eyes. In case of contact, rinse eyes thoroughly with water.

Discontinue use if irritation occurs.

Inactive Ingredients

Aloe Barbadensis Leaf Juice, Blue 1, Cocamidopropyl Hydroxysultaine, Disodium EDTA, Ethylhexylglycerin, Fragrance, Glycereth-26, Isopropyl Alcohol, Phenoxyethanol, Sodium Chloride, Sodium Hydroxide, Sodium Laureth Sulfate, Styrene/Acrylates Copolymer, Water, Yellow 5